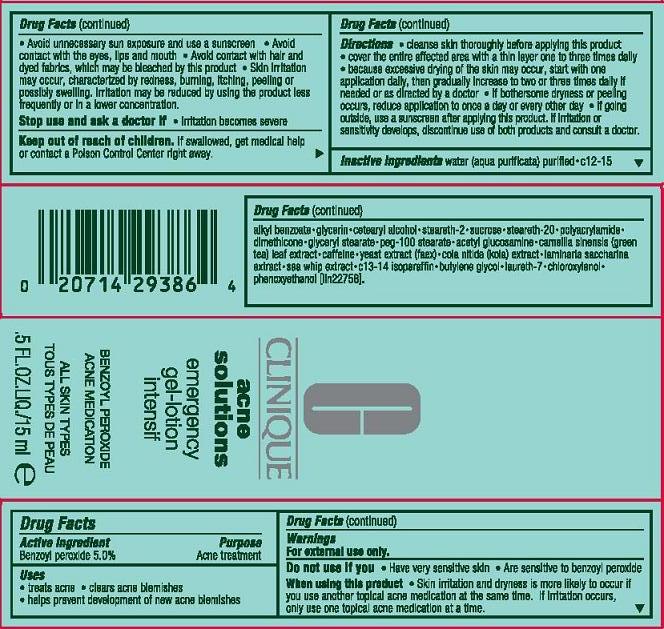 DRUG LABEL: ACNE SOLUTIONS
NDC: 49527-718 | Form: LOTION
Manufacturer: CLINIQUE LABORATORIES INC
Category: otc | Type: HUMAN OTC DRUG LABEL
Date: 20110721

ACTIVE INGREDIENTS: BENZOYL PEROXIDE 2.5 mL/100 mL
INACTIVE INGREDIENTS: WATER; ALKYL (C12-15) BENZOATE; GLYCERIN; CETOSTEARYL ALCOHOL; STEARETH-2; SUCROSE; STEARETH-20; DIMETHICONE; GLYCERYL MONOSTEARATE; PEG-100 STEARATE; GREEN TEA LEAF; CAFFEINE; YEAST; COLA NITIDA SEED; PSEUDOPTEROGORGIA ELISABETHAE; C13-14 ISOPARAFFIN; BUTYLENE GLYCOL; LAURETH-7; CHLOROXYLENOL; PHENOXYETHANOL

ACTIVE INGREDIENT: BENZOYL PEROXIDE 0.5%

INACTIVE INGREDIENT

water [] c12-15 alkyl benzoate [] glycerin [] cetearyl alcohol [] steareth-2 [] sucrose [] steareth-20 [] polyacrylamide [] dimethicone [] glyceryl stearate [] peg-100 stearate [] acetyl glucosamine [] camellia sinensis leaf extract [] caffeine [] yeast extract (faex) [] cola nitida extract [] laminaria saccharina extract [] sea whip extract [] c13-14 isoparaffin [] butylene glycol [] laureth-7 [] chloroxylenol [] phenoxyethanol

USES:

- TREATS ACNE
- CLEARS ACNE BLEMISHES
- HELPS PREVENT DEVELOPMENT OF NEW ACNE BLEMISHES

WARNINGS

WARNING: FOR EXTERNAL USE ONLY

DO NOT USE IF YOU

- HAVE VERY SENSITIVE SKIN
- ARE SENSITIVE TO BENZOYL PEROXIDE

WHEN USING THIS PRODUCT

- SKIN IRRITATION AND DRYNESS IS MORE LIKELY TO OCCUR IF YOU USE ANOTHER TOPICAL ACNE MEDICATION AT THIS TIME. IF IRRITATION OCCURS, USE ONLY ONE TOPICAL ACNE MEDICATION AT AT TIME
- AVOID UNNECESSARY SUN EXPOSURE AND USE A SUNSCREEN
- AVOID CONTACT WITH THE EYES, LIPS, AND MOUTH
- AVOID CONTACT WITH HAIR AND DYED FABRICS, WHICH MAY BE BLEACHED BY THIS PRODUCT
- SKIN IRRITATION MAY OCCUR, CHARACTERIZED BY REDNESS, BURNING, ITCHING, PEELING OR POSSIBLY SWELLING. IRRITATION MAY BE REDUCED BY USING THE PRODUCT LESS FREQUENTLY OR IN A LOWER CONCENTRATION

STOP USE AND ASK A DOCTOR IF

- IRRITATION BECOMES SEVERE

KEEP OUT OF REACH OF CHILDREN

IF SWALLOWED, GET MECICAL HELP OR CONTACT A POISON CONTROL CENTER RIGHT AWAY.

DIRECTIONS:

- CLEANS SKIN THOROUGHLY BEFORE APPLYING THIS PRODUCT
- COVER THE ENTIRE AFFECTED AREA WITH A THIN LAYER ONE TO THREE TIMES DAILY
- BECAUSE EXCESSIVE DRYING OF THE SKIN MAY OCCUR, START WITH ONE APPLICATION DAILY, THEN GRADUALLY INCREASE TO TWO OR THREE TIMES DAILY IF NEEDED OR AS DIRECTED BY A DOCTOR
- IF BOTHERSOME DRYNESS OR PEELING OCCURS, REDUCE APPLICATION TO ONCE A DOY OR EVERY OTHER DAY
- IF GOING OUTSIDE, USE A SUNSCREEN AFTER APPLYING THIS PRODUCT. IF IRRITATION OR SENSITIVITY DEVELOPS, DISCONTINUE USE OF BOTH PRODUCTS AND CONSULT A DOCTOR
- FOR BEST RESULTS, USE AFTER ACNE SOLUTIONS CLEANSING FOAM AND CLARIFYING LOTION

DOSAGE AND ADMINISTRATION

COVER THE ENTIRE AFFECTED AREA WITH A THIN LAYER ONE TO THREE TIMES DAILY

PACKAGE LABEL

PRINCIPAL DISPLAY PANEL:

CLINIQUE
ACNE SOLUTIONS
EMERGENCY
GEL-LOTION
BENZOYL PEROXIDE
ACNE MEDICATION
ALL SKIN TYPES
0.5 FL OZ LIQ. / 15 ML
CLINIQUE LABORATORIES DIST
NEW YORK, NEW YORK 10022